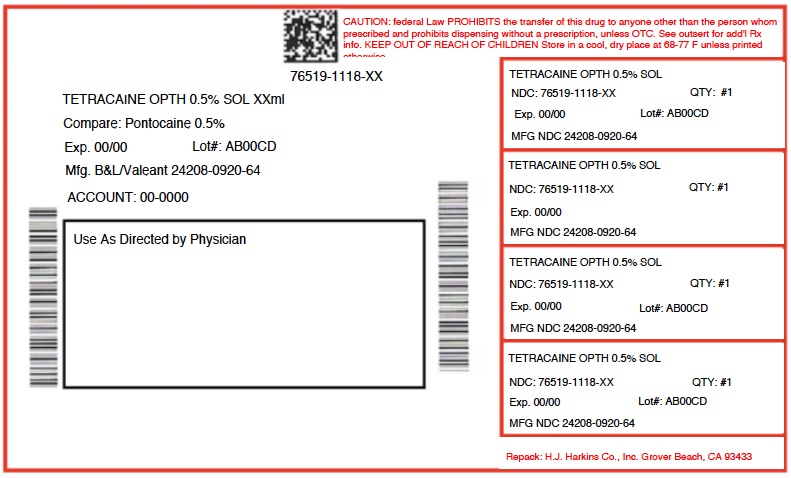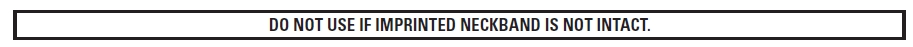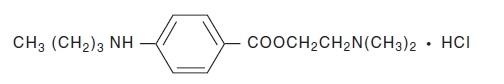 DRUG LABEL: TETRACAINE HYDROCHLORIDE
NDC: 76519-1118 | Form: SOLUTION
Manufacturer: H.J. Harkins Company, Inc.
Category: prescription | Type: HUMAN PRESCRIPTION DRUG LABEL
Date: 20180824

ACTIVE INGREDIENTS: TETRACAINE HYDROCHLORIDE 5 mg/1 mL

1118

DESCRIPTION

Tetracaine Hydrochloride is a sterile aqueous topical anesthetic ophthalmic solution. The active ingredient is represented by the chemical structure:

C15H24N2O2·HCI
Mol. wt. 300.83

Benzoic acid, 4-[butylamino]-, 2-[dimethylamino]ethyl ester, monohydrochloride.

EACH mL CONTAINS: ACTIVE: Tetracaine Hydrochloride 5 mg (0.5%); INACTIVES: Boric Acid, Potassium Chloride, Edetate Disodium and Purified Water. Sodium Hydroxide and/or Hydrochloric Acid may be added to adjust pH (3.7 - 6.0). PRESERVATIVE ADDED: Chlorobutanol 0.4%.

CLINICAL PHARMACOLOGY

Topical anesthetics stabilize the neuronal membrane and prevent the initiation and transmission of nerve impulses, thereby effecting local anesthesia. The onset of anesthesia usually begins within 30 seconds and lasts a relatively short period of time.

INDICATIONS AND USAGE

For procedures in which a rapid and short-acting topical ophthalmic anesthetic is indicated such as in tonometry, gonioscopy, removal of corneal foreign bodies, conjunctival scraping for diagnostic purposes, suture removal from the cornea, other short corneal and conjunctival procedures.

CONTRAINDICATIONS

Should not be used by the patient without physician supervision, or in those persons showing hypersensitivity to any component of this preparation. This product should never be prescribed for the patient’s own use.

WARNINGS

Prolonged use results in diminished duration of anesthesia and retarded healing. This may cause the drug to be used more frequently creating a “vicious circle.” Subsequent corneal infection and/or corneal opacification with accompanying permanent visual loss or corneal perforation may occur.

PRECAUTIONS

FOR TOPICAL USE ONLY—NOT FOR INJECTION. To prevent contaminating the dropper tip and solution, care should be taken not to touch the eyelids or surrounding area with the dropper tip. Patient should be advised not to touch or rub the eye(s) until the effect of the anesthetic has worn off.

Information to the Patient:

After instillation of this product, the surface of the eye is insensitive and can be scratched without feeling it. Do not rub eye. Do not instill this product repeatedly because severe eye damage may occur.

DO NOT USE IF SOLUTION CONTAINS CRYSTALS, OR IS CLOUDY OR DISCOLORED.

ADVERSE REACTIONS

Transient symptoms (signs) such as stinging, burning and conjunctival redness may occur. A rare, severe, immediate allergic cornea reaction has been reported, characterized by acute diffuse epithelial keratitis with filament formation and/or sloughing of large areas of necrotic epithelium, diffuse stromal edema, descemetitis and iritis.

DOSAGE AND ADMINISTRATION

For tonometry and other procedures of short duration, instill one or two drops just prior to evaluation. For minor surgical procedures such as foreign body or suture removal, administer one to two drops every five to ten minutes for one to three instillations. For prolonged anesthesia as in cataract extraction, instill one or two drops in the eye(s) every five to ten minutes for three to five doses.

HOW SUPPLIED

Tetracaine Hydrochloride Ophthalmic Solution USP, 0.5% is supplied in a plastic bottle with a controlled drop tip in the following size:

15 mL

STORAGE AND HANDLING

Store between 15°-25°C (59°-77°F).

KEEP TIGHTLY CLOSED.

KEEP OUT OF REACH OF CHILDREN.